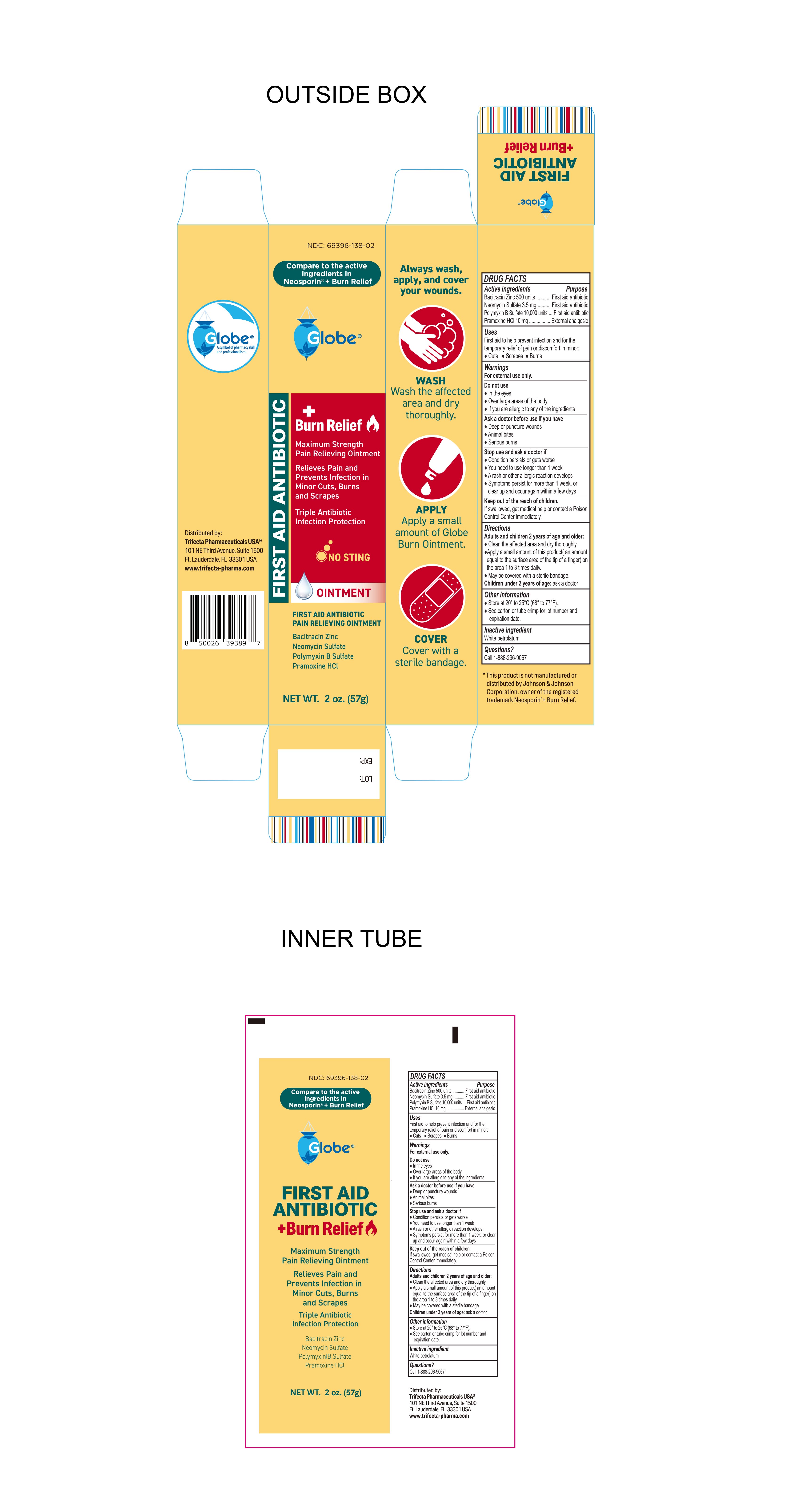 DRUG LABEL: First Aid Antibiotic plus Burn Relief
NDC: 69396-138 | Form: OINTMENT
Manufacturer: Trifecta Pharmaceuticals USA LLC
Category: otc | Type: HUMAN OTC DRUG LABEL
Date: 20241218

ACTIVE INGREDIENTS: PRAMOXINE HYDROCHLORIDE 10 mg/1 g; POLYMYXIN B SULFATE 10000 [USP'U]/1 g; BACITRACIN ZINC 500 [USP'U]/1 g; NEOMYCIN SULFATE 3.5 mg/1 g
INACTIVE INGREDIENTS: WHITE PETROLATUM

Globe First Aid Antibiotic Plus Burn Relief

Active Ingredient

Pramoxine HCI

Purpose Section

External Analgesic

Active Ingredient

Polymyxin B Sulfate

Purpose

First Aid Antibiotic

Active Ingredient

Bacitracin Zinc

Purpose

First Aid Antibiotic

ACTIVE INGREDIENT

Neomycin Sulfate

Purpose

First Aid Antibiotic

Uses

First Aid to help prevent infection and for the temporary relief of pain or discomfort in minor cuts, scrapes and burns.

Warnings

For external Use Only

Do Not Use

- In the eyes
- Over large areas of the body
- If you are allergic to any of the ingredients

Ask Doctor before use if you have

- Deep or puncture wounds
- Animal Bites
- Serious Burns

Stop Use and ask a doctor if

- Condition persists or gets worse
- You need to use longer than 1 week
- A rash or other allergic reaction develops
- symptoms persist for more than 1 week or clear up and occur again within a few days

Directions

Adults and children 2 years of age and older:

- Clean the affected area and dry thoroughly.
- Apply a small amount of this product , an mount equal to the surgace area of the tip of a finger) on the area 1 to 3 times daily
- May be covered with a sterile bandage

Children under 2 years old: ask a doctor

Inactive Ingredients

White Petrolatum

Questions

Call 1-888-296-9067

Storage Information

- Store at 20° to 25°C (68° to 77°F).
- See carton or tube crimp for lot number and expiration date

Keep out of reach of children

If swallowed, get medical help or contact a Poison Control Center immediately.

Other Information

Distributed By:

Trifecta Pharmaceuticals USA®

101 NE Third Avenue, Suite 1500

Fort Lauderdale, FL. 33301 USA

www.trifecta-pharma.com